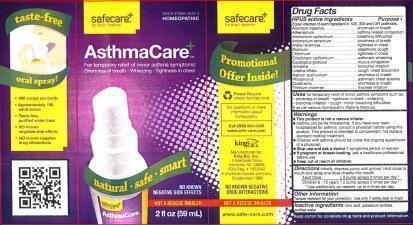 DRUG LABEL: AsthmaCare
NDC: 57955-7044 | Form: LIQUID
Manufacturer: King Bio Inc.
Category: homeopathic | Type: HUMAN OTC DRUG LABEL
Date: 20140401

ACTIVE INGREDIENTS: ACONITUM NAPELLUS 10 [hp_X]/29.6 mL; EPINEPHRINE 10 [hp_X]/29.6 mL; AMMONIUM CARBONATE 10 [hp_X]/29.6 mL; ANTIMONY POTASSIUM TARTRATE 10 [hp_X]/29.6 mL; ARALIA RACEMOSA ROOT 10 [hp_X]/29.6 mL; BROMINE 10 [hp_X]/29.6 mL; CHLORINE 10 [hp_X]/29.6 mL; ERIODICTYON CALIFORNICUM LEAF 10 [hp_X]/29.6 mL; EUCALYPTUS GLOBULUS LEAF 10 [hp_X]/29.6 mL; GRINDELIA HIRSUTULA WHOLE 10 [hp_X]/29.6 mL; LOBELIA INFLATA 10 [hp_X]/29.6 mL; SODIUM SULFATE 10 [hp_X]/29.6 mL; PHOSPHORUS 10 [hp_X]/29.6 mL; ASPIDOSPERMA QUEBRACHO-BLANCO BARK 10 [hp_X]/29.6 mL; TRIFOLIUM PRATENSE FLOWER 10 [hp_X]/29.6 mL
INACTIVE INGREDIENTS: CITRIC ACID MONOHYDRATE; POTASSIUM SORBATE; WATER

AsthmaCare

HPUS active ingredients

_________________________________________________________________________________________________________________

Equal volumes of each ingredient in 10X, 30X, and LM1 potencies.

Aconitum napellus, Adrenalinum, Ammonium carbonicum, Antimonium tartaricum, Aralia racemosa, Bromium, Chlorinum, Eriodictyon Californicum, Eucalyptus globulus, Grindelia, Lobelia inflata, Natrum sulphuricum, Phosphorus, Quebracho, Trifolium pratense.

HPUS active ingredients Purpose †

Equal volumes of each ingredient in 10X, 30X, and LM1 potencies.

Aconitum napellus....................................................shortness of breath

Adrenalinum.............................................................asthma related congestion

Ammonium carbonicum.............................................breathing difficulties

Antimonium tararicum...............................................shortmess of breath

Aralia racemosa........................................................tightness in chest

Bromium..................................................................spasmodic cough

Chlorinum................................................................tightness in chest

Eriodictyon californicum.............................................asthmatic wheezing

Eucalyptus globulus..................................................mucus congestion

Grindelia.................................................................bronchial irritation

Lobelia inflata..........................................................cough, chest discomfort

Natrum sulphuricum.................................................shortness of breath

Phosphorus.............................................................asthmatic chest spasms

Quebracho..............................................................shortness of breath

Trifolium pratense....................................................tracheal irritation

Uses

For temporary relief or minor asthma symptoms such as:

- shortness of breath
- tightness in chest
- wheezing
- bronchial irritation
- cough
- minor breathing difficulties

† as per various homeopathic Materia Medicas.

Warnings

- This product is not a rescue inhaler.
- Asthma can be life threatening. If you have ever been hospitalized for asthma, consult a physician before using this product. This product is intended to complement, not replace, standard medical treatment.
- Children with asthma should be under the ongoing supervision of a physician.
- Stop use and ask a doctor if symptoms persist or worsen.
- If pregnant or breast-feeding, ask a healthcare professional before use.

- Keep out of reach of children.

Directions

Initially, depress pump until primed. Hold close to mouth and spray one dose directly into mouth.

Adult Dose 3 pump sprays 3 times per day.

Children 6-12 years 2 pump sprays 3 times per day.

Use additionally as needed, up to 6 times per day.

Other information:

Tamper resistant for your protection. Use only if safety seal is intact.

INACTIVE INGREDIENT

Inactive Ingredients: Citric acid, Potassium sorbate and Purified water.